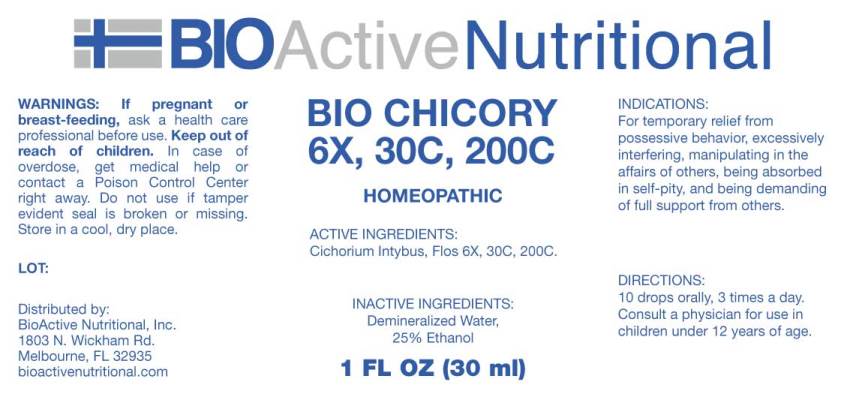 DRUG LABEL: Bio Chicory
NDC: 43857-0495 | Form: LIQUID
Manufacturer: BioActive Nutritional, Inc.
Category: homeopathic | Type: HUMAN OTC DRUG LABEL
Date: 20180904

ACTIVE INGREDIENTS: CICHORIUM INTYBUS FLOWER 6 [hp_X]/1 mL
INACTIVE INGREDIENTS: WATER; ALCOHOL

Drug Facts:

ACTIVE INGREDIENTS:

Cichorium Intybus, Flos 6X, 30C, 200C.

INDICATIONS:

For temporary relief from possessive behavior, excessively interfering, manipulating in the affairs of others, being absorbed in self-pity, and being demanding of full support from others.

WARNINGS:

If pregnant or breast-feeding, ask a health care professional before use.

Keep out of reach of children. In case of overdose, get medical help or contact a Poison Control Center right away.

Do not use if tamper evident seal is broken or missing.

Store in cool, dry place.

Keep out of reach of children. In case of overdose, get medical help or contact a Poison Control Center right away.

DIRECTIONS:

10 drops orally, 3 times a day. Consult a physician for use in children under 12 years of age.

INDICATIONS:

For temporary relief from possessive behavior, excessively interfering, manipulating in the affairs of others, being absorbed in self-pity, and being demanding of full support from others.

INACTIVE INGREDIENTS:

Demineralized Water, 25% Ethanol.

QUESTIONS:

Distributed by:
BioActive Nutritional, Inc.
1803 N. Wickham Rd.
Melbourne, FL 32935
bioactivenutritional.com

PACKAGE DISPLAY LABEL:

BIOActive Nutritional

BIO CHICORY

6X, 30C, 200C

HOMEOPATHIC

1 FL OZ (30 ml)